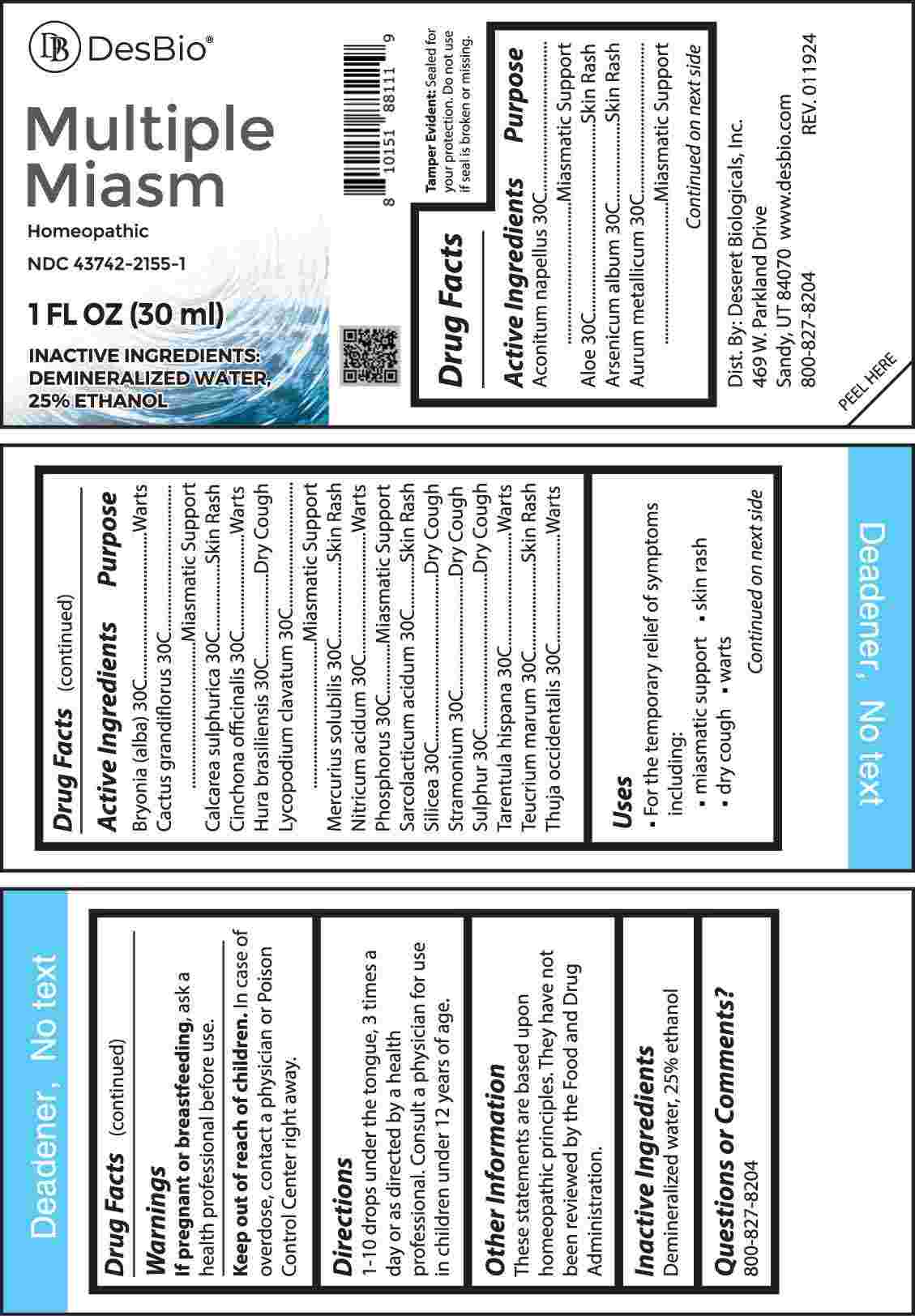 DRUG LABEL: Multiple Miasm
NDC: 43742-2155 | Form: LIQUID
Manufacturer: Deseret Biologicals, Inc.
Category: homeopathic | Type: HUMAN OTC DRUG LABEL
Date: 20240521

ACTIVE INGREDIENTS: ACONITUM NAPELLUS WHOLE 30 [hp_C]/1 mL; ALOE 30 [hp_C]/1 mL; ARSENIC TRIOXIDE 30 [hp_C]/1 mL; GOLD 30 [hp_C]/1 mL; BRYONIA ALBA ROOT 30 [hp_C]/1 mL; SELENICEREUS GRANDIFLORUS STEM 30 [hp_C]/1 mL; CALCIUM SULFATE ANHYDROUS 30 [hp_C]/1 mL; CINCHONA OFFICINALIS BARK 30 [hp_C]/1 mL; HURA CREPITANS SAP 30 [hp_C]/1 mL; LYCOPODIUM CLAVATUM SPORE 30 [hp_C]/1 mL; MERCURIUS SOLUBILIS 30 [hp_C]/1 mL; NITRIC ACID 30 [hp_C]/1 mL; PHOSPHORUS 30 [hp_C]/1 mL; LACTIC ACID, L- 30 [hp_C]/1 mL; SILICON DIOXIDE 30 [hp_C]/1 mL; DATURA STRAMONIUM 30 [hp_C]/1 mL; SULFUR 30 [hp_C]/1 mL; LYCOSA TARANTULA 30 [hp_C]/1 mL; TEUCRIUM MARUM WHOLE 30 [hp_C]/1 mL; THUJA OCCIDENTALIS LEAFY TWIG 30 [hp_C]/1 mL
INACTIVE INGREDIENTS: WATER; ALCOHOL

DRUG FACTS:

ACTIVE INGREDIENTS:

Aconitum Napellus 30C, Aloe 30C, Arsenicum Album 30C, Aurum Metallicum 30C, Bryonia (Alba) 30C, Cactus Grandiflorus 30C, Calcarea Sulphurica 30C, Cinchona Officinalis 30C, Hura Brasiliensis 30C, Lycopodium Clavatum 30C, Mercurius Solubilis 30C, Nitricum Acidum 30C, Phosphorus 30C, Sarcolacticum Acidum 30C, Silicea 30C, Stramonium 30C, Sulphur 30C, Tarentula Hispana 30C, Teucrium Marum 30C, Thuja Occidentalis 30C.

PURPOSE:

Aconitum Napellus – Miasmatic Support, Aloe – Skin Rash, Arsenicum Album – Skin Rash, Aurum Metallicum – Miasmatic Support, Bryonia (Alba) - Warts, Cactus Grandiflorus – Miasmatic Support, Calcarea Sulphurica – Skin Rash, Cinchona Officinalis - Warts, Hura Brasiliensis – Dry Cough, Lycopodium Clavatum – Miasmatic Support, Mercurius Solubilis – Skin Rash, Nitricum Acidum - Warts, Phosphorus – Miasmatic Support, Sarcolacticum Acidum – Skin Rash, Silicea – Dry Cough, Stramonium – Dry Cough, Sulphur – Dry Cough, Tarentula Hispana - Warts, Teucrium Marum – Skin Rash, Thuja Occidentalis - Warts

USES:

• For the temporary relief of symptoms including:

• miasmatic support • skin rash • dry cough • warts

These statements are based upon homeopathic principles. They have not been reviewed by the Food and Drug Administration.

WARNINGS:

If pregnant or breast-feeding, ask a health professional before use.

Keep out of reach of children. In case of overdose contact a physician or Poison Control Center right away.

Tamper Evident: Sealed for your protection. Do not use if seal is broken or missing.

KEEP OUT OF REACH OF CHILDREN:

In case of overdose, contact a physician or Poison Control Center right away.

DIRECTIONS:

1-10 drops under the tongue, 3 times a day or as directed by a health professional. Consult a physician for use in children under 12 years of age.

INACTIVE INGREDIENTS:

Demineralized water, 25% ethanol

QUESTIONS:

Dist. By: Deseret Biologicals, Inc.

469 W. Parkland Drive

Sandy, UT 84070

www.desbio.com

800-827-8204

PACKAGE LABEL DISPLAY:

DesBio

Multiple

Miasm

Homeopathic

NDC 43742-2155-1

1 FL OZ (30 ml)